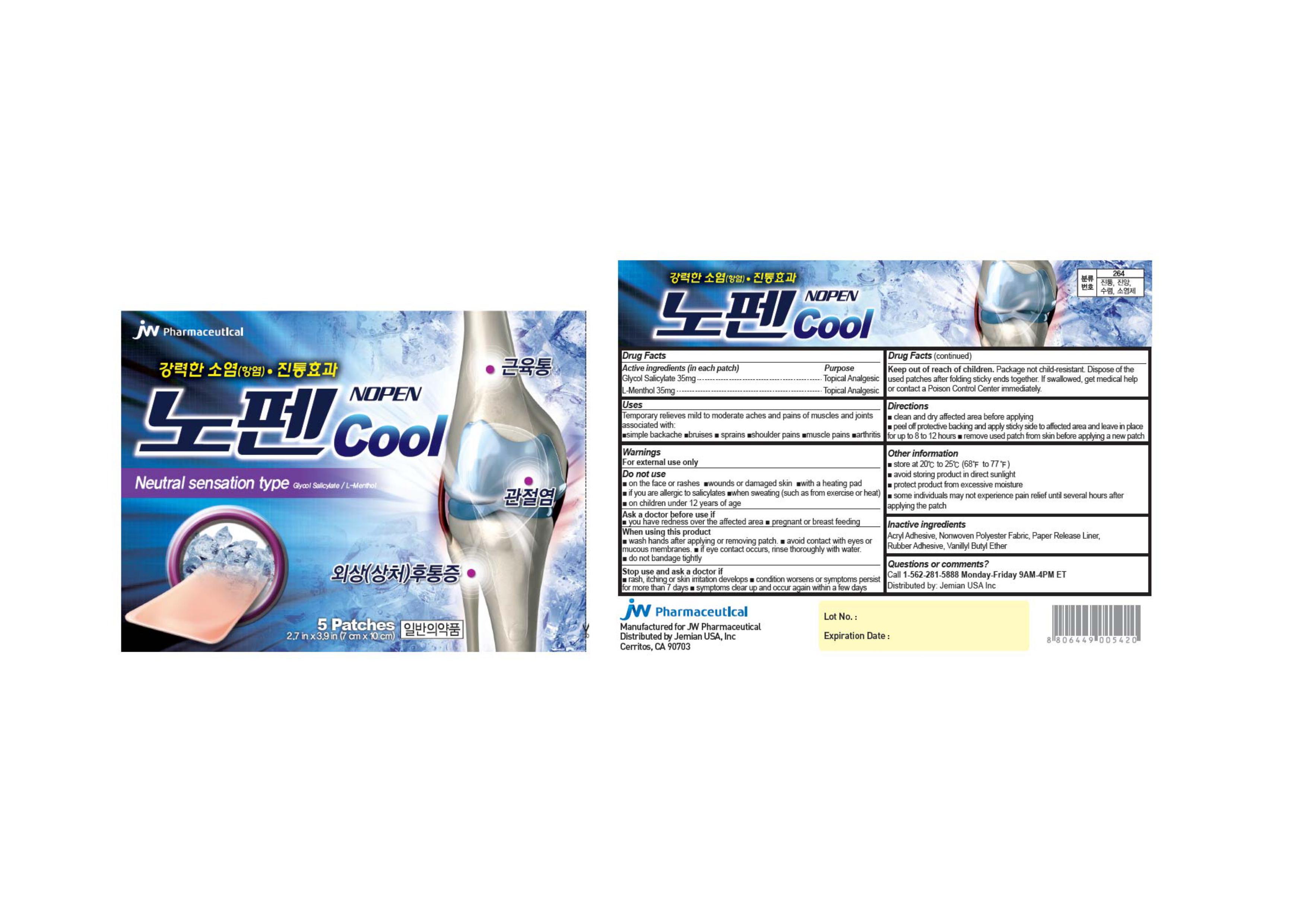 DRUG LABEL: NOPEN COOL
NDC: 69365-006 | Form: PATCH
Manufacturer: JW HOLDINGS CORPORATION
Category: otc | Type: HUMAN OTC DRUG LABEL
Date: 20180820

ACTIVE INGREDIENTS: GLYCOL SALICYLATE 35 mg/1 1; MENTHOL, UNSPECIFIED FORM 35 mg/1 1
INACTIVE INGREDIENTS: LOW DENSITY POLYETHYLENE; 2-ETHYLHEXYL ACRYLATE; VANILLYL BUTYL ETHER; POLYETHYLENE TEREPHTHALATE (INTRINSIC VISCOSITY 0.70-1.00); POWDERED CELLULOSE

NOPEN COOL

Active Ingredients (in each patch)

Glycol Salicylate 35mg

L-Menthol 35mg

Purpose

Topical Analgesic

Uses

Temporary relieves mild to moderate aches and pains of muscles and joints associated with:

■simple backache ■bruises ■sprains ■shoulder pains ■muscle pains ■arthritis

Warnings

For external use only

Do not use

■on the face or rashes ■wounds or damaged skin ■with a heating pad ■if you are allergic to salicylates

■when sweating (Such as from exercise or heat) ■on children under 12 years of age

Ask a doctor before use if

■ you have redness over the affected area ■ pregnant or breast feeding

When using this product

■ wash hands after applying or removing patch. ■ avoid contact with eyes or mucous membranes. ■ if eye contact occurs, rinse thoroughly with water. ■ do not bandage tightly

Stop use and ask a doctor if

■ rash, itching or skin irritation develops ■ condition worsens or symptoms persist for more than 7 days ■ symptoms clear up and occur again within a few days

Keep out of reach of children

Package not child-resistant. Dispose of the used patches after folding sticky ends together. If swallowed, get medical help or contact a Poison Control Center immediately.

Directions

■ clean and dry affected area before applying

■ peel off protective backing and apply sticky side to affected area and leave in place for up to 8 to 12 hours

■ remove used patch from skin before applying a new patch

Other Information

■ store at 20℃ to 25℃ (68℉ to 77℉)

■ avoid storing product in direct sunlight

■ protect product from excessive moisture

■ some individuals may not experience pain relief until several hours after applying the patch

Inactive ingredients

Acryl Adhesive, Nonwoven Polyester Fabric, Paper Release Liner, Rubber Adhesive, Vanillyl Butyl Ether

Questions or comments?

Call 1-562-281-5888 Monday-Friday 9AM-4PM ET

Distributed by: Jemian USA Inc

Principal Display Panel-5 Patches

JW Pharmaceutical

NOPEN

Cool

Neutral sensation type Glycol Salicylate/ L-Menthol

5 Patches

2.7 in x 3.9 in (7 cm x 10 cm)